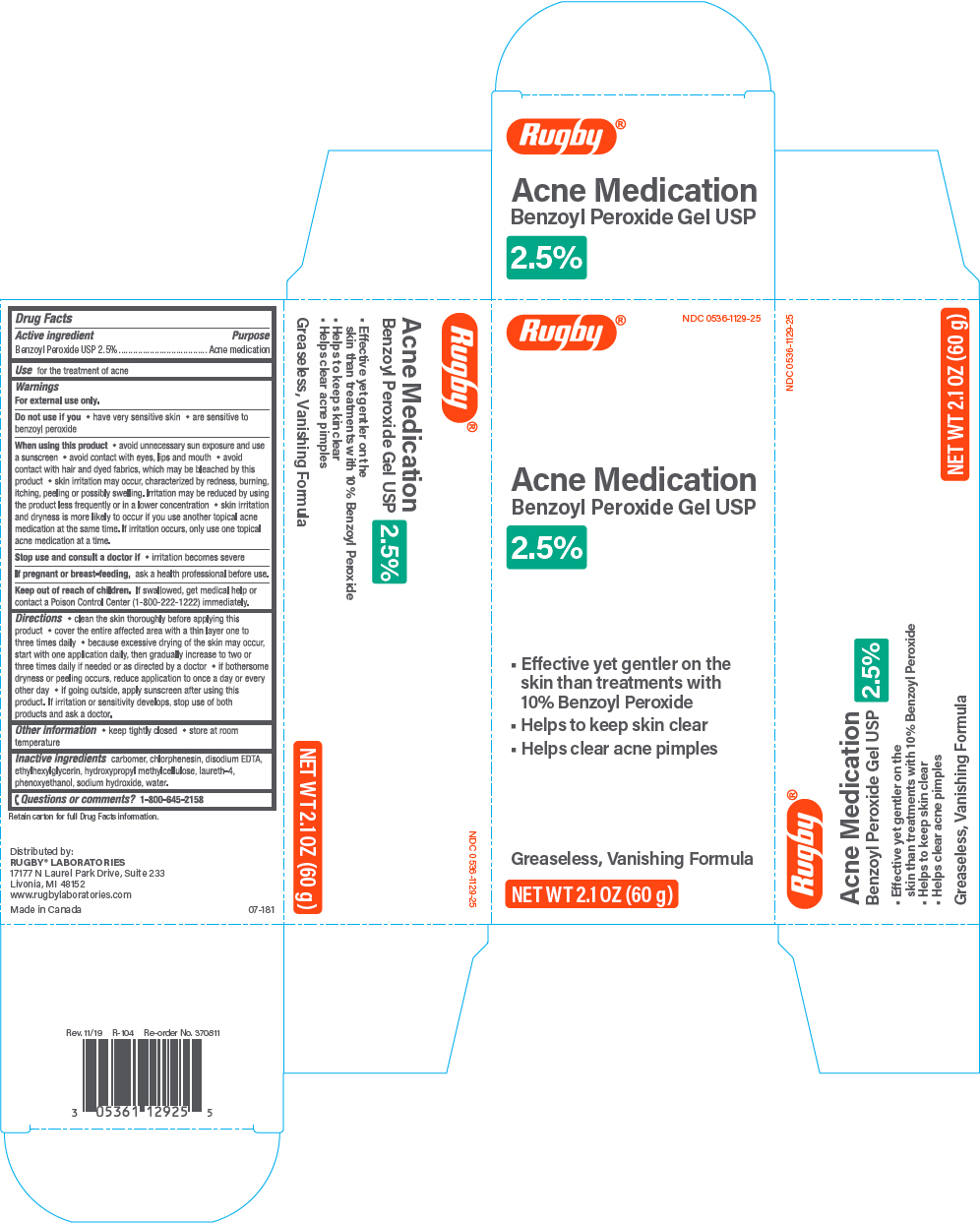 DRUG LABEL: Rugby Acne Medication Benzoyl Peroxide
NDC: 0536-1129 | Form: GEL
Manufacturer: Rugby Laboratories
Category: otc | Type: HUMAN OTC DRUG LABEL
Date: 20240301

ACTIVE INGREDIENTS: Benzoyl Peroxide 25 mg/1 g
INACTIVE INGREDIENTS: CARBOXYMETHYLCELLULOSE SODIUM, UNSPECIFIED; Chlorphenesin; Edetate Disodium; Ethylhexylglycerin; Hypromellose, Unspecified; Laureth-4; Phenoxyethanol; Sodium Hydroxide; Water

Rugby® Acne Medication Benzoyl Peroxide Gel USP 2.5%

Drug Facts

Active ingredient

Benzoyl Peroxide USP 2.5%

Purpose

Acne medication

Use

for the treatment of acne

Warnings

For external use only.

Do not use if you

- have very sensitive
- are sensitive to benzoyl peroxide

When using this product

- avoid unnecessary sun exposure and use a sunscreen
- avoid contact with eyes, lips and mouth
- avoid contact with hair or dyed fabrics, which may be bleached by this product
- skin irritation may occur, characterized by redness, burning, itching, peeling, or possibly swelling. Irritation may be reduced by using the product less frequently or in a lower concentration.
- skin irritation and dryness is more likely to occur if you use another topical acne medication at the same time. If irritation occurs, only use one topical acne medication at a time.

Stop use and consult a doctor if

- irritation becomes severe

PREGNANCY OR BREAST FEEDING

If pregnant or breast-feeding, ask a health professional before use.

Keep out of reach of children. If swallowed, get medical help or contact a Poison Control Center (1-800-222-1222) immediately.

Directions

- clean the skin thoroughly before applying this product
- cover the entire affected area with a thin layer one to three times daily
- because excessive drying of the skin may occur, start with one application daily, then gradually increase to two or three times daily if needed or as directed by a doctor
- if bothersome dryness or peeling occurs, reduce application to once a day or every other day
- if going outside, apply sunscreen after using this product. If irritation or sensitivity develops, stop use of both products and ask a doctor.

Other information

- keep tightly closed
- store at room temperature

Inactive ingredients

carbomer, chlorphenesin, disodium EDTA, ethylhexylglycerin, hydroxyl methylcellulose, laureth-4, phenoxyethanol, sodium hydroxide, water.

Questions or comments?

1-800-645-2158

Distributed by:
RUGBY® LABORATORIES
17177 N Laurel Park Drive, Suite 233
Livonia, MI 48152

PRINCIPAL DISPLAY PANEL - 60 g Tube Carton

Rugby®

NDC 0536-1129-25

Acne Medication
Benzoyl Peroxide Gel USP

2.5%

- Effective yet gentler on the
  skin than treatments with
  10% Benzoyl Peroxide
- Helps to keep skin clear
- Helps clear acne pimples

Greaseless, Vanishing Formula

NET WT 2.1 OZ (60 g)